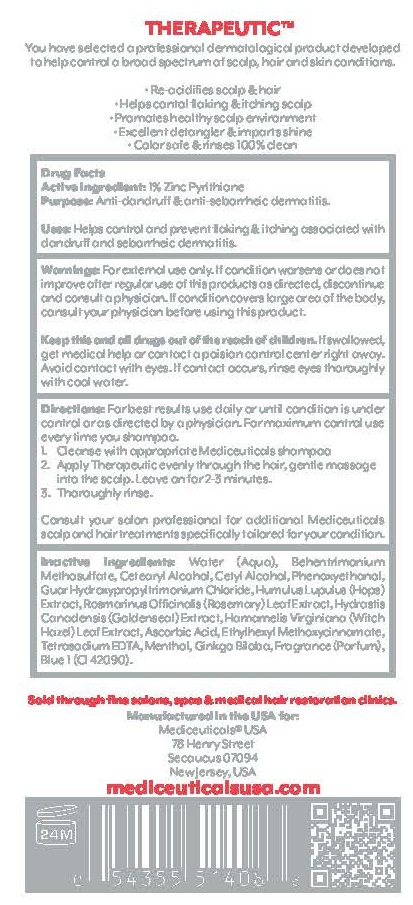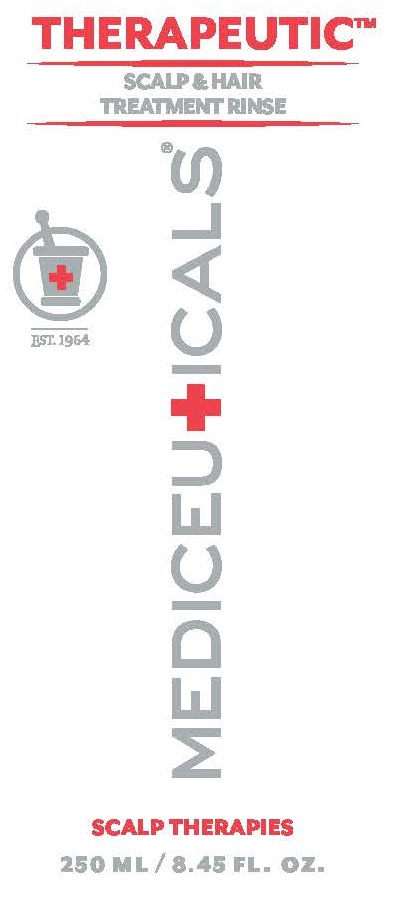 DRUG LABEL: THERAPEUTIC
NDC: 59279-515 | Form: RINSE
Manufacturer: Mediceutical Laboratories, LTD
Category: otc | Type: HUMAN OTC DRUG LABEL
Date: 20220113

ACTIVE INGREDIENTS: PYRITHIONE ZINC 1 g/100 mL
INACTIVE INGREDIENTS: WATER; BEHENTRIMONIUM CHLORIDE; CETOSTEARYL ALCOHOL; CETYL ALCOHOL; PHENOXYETHANOL; GUAR HYDROXYPROPYLTRIMONIUM CHLORIDE (1.7 SUBSTITUENTS PER SACCHARIDE); HOPS; ROSEMARY; GOLDENSEAL; WITCH HAZEL; ASCORBIC ACID; OCTINOXATE; EDETATE SODIUM TETRAHYDRATE; MENTHOL; GINKGO BILOBA WHOLE; FD&C BLUE NO. 1

Mediceutical Laboratories - THERAPEUTIC SCALP & HAIR TREATMENT RINSE (59279-515)

Active ingredient

Pyrithione Zinc 1%

Purpose

anti-dandruff, anti-seborrheic, dermatitis

Uses

HELPS CONTROL AND PREVENT FLAKING AND ITCHING ASSOCIATED WITH DANDRUFF AND SEBORRHEIC DERMATITUS.

Warnings

For external use only. If condition worsens or does not improve after regular use of this product as directed, discontinue and consult a physician. If condition covers a large area of the body, consult your physician before using this product.

Avoid contact with eyes. If contact occurs, rinse eyes thoroughly with cool water.

Keep this and all drugs out of reach of children.

If swallowed, get medical help or contact a Poison Control Center right away.

Directions

For best results use daily or until conditionis iunder control or as directed by a physician. For maximum control use every time you shampoo.

1. Cleanse with appropriate Mediceuticals® shampoo
2. Work ample amount of TherapeuticTM Scalp and Hair Treatment Rinse evenly through hair, gently massage onto the scalp, leave on 1-2 minutes
3. Thoroughly rinse

Consult your Salon professional for additional Mediceuticals® scalp and hair treatment specifically tailored for your condition.

Inactive ingredients

WATER (AQUA), BEHENTRIMONIUM METHOSULFATE, CETEARYL ALCOHOL, CETYL ALCOHOL, PHENOXYETHANOL, GUAR HYDROXYPROPYLTRIMONIUM CHLORIDE, HUMULUS LUPULUS (HOPS) EXTRACT, ROSMARINUS OFFICINALIS (ROSEMARY) LEAF EXTRACT, HYDRASTIS CANADENSIS (GOLDENSEAL) EXTRACT, HAMAMELIS VIRGINIANA (WITCH hAZEL) LEAF EXTRACT, ASCORBIC ACID, ETHYLHEXYL METHOXYCINNAMATE, TETRASODIUM EDTA, MENTHOL, GINKGO BILOBA, FRAGRANCE (PARFUM), BLUE 1 (CI 42090).